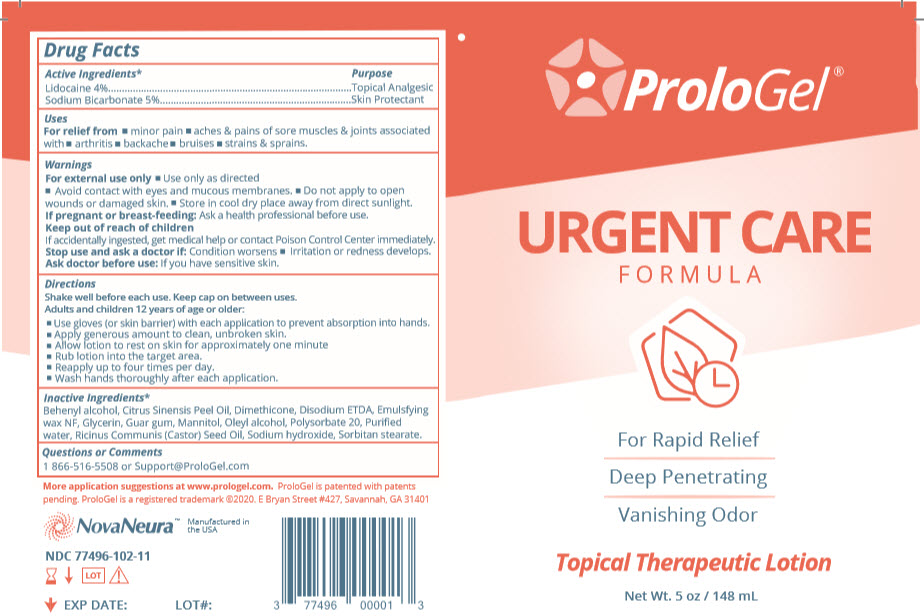 DRUG LABEL: ProloGel Urgent Care
NDC: 77496-102 | Form: LOTION
Manufacturer: Nova Neura, LLC
Category: otc | Type: HUMAN OTC DRUG LABEL
Date: 20210903

ACTIVE INGREDIENTS: LIDOCAINE 0.04 mg/1 mL; SODIUM BICARBONATE 0.05 mg/1 mL
INACTIVE INGREDIENTS: DOCOSANOL; SHEA BUTTER; ORANGE OIL, COLD PRESSED; DIMETHICONE; EDETATE DISODIUM; GLYCERIN; GUAR GUM; MANNITOL; OLEYL ALCOHOL; POLYSORBATE 20; WATER; CASTOR OIL; SODIUM HYDROXIDE; SORBITAN MONOSTEARATE

ProloGel® Urgent Care

Drug Facts

ACTIVE INGREDIENT

Active Ingredients* | Purpose
Lidocaine 4% | Topical Analgesic
Sodium Bicarbonate 5% | Skin Protectant

Uses

For relief from

- minor pain
- aches & pains of sore muscles & joints associated with
  - arthritis
  - backache
  - bruises
  - strains & sprains.

Warnings

For external use only

- Use only as directed
- Avoid contact with eyes and mucous membranes.
- Do not apply to open wounds or damaged skin.
- Store in cool dry place away from direct sunlight.

If pregnant or breast-feeding

Ask a health professional before use.

Keep out of reach of children

If accidentally ingested, get medical help or contact Poison Control Center immediately.

Stop use and ask a doctor if

Condition worsens

- Irritation or redness develops.

Ask doctor before use

If you have sensitive skin.

Directions

Shake well before each use. Keep cap on between uses.

Adults and children 12 years of age or older:

- Use gloves (or skin barrier) with each application to prevent absorption into hands.
- Apply generous amount to clean, unbroken skin.
- Allow lotion to rest on skin for approximately one minute
- Rub lotion into the target area.
- Reapply up to four times per day.
- Wash hands thoroughly after each application.

Inactive Ingredients*

Behenyl alcohol, Citrus Sinensis Peel Oil, Dimethicone, Disodium ETDA, Emulsfying wax NF, Glycerin, Guar gum, Mannitol, Oleyl alcohol, Polysorbate 20, Puriﬁed water, Ricinus Communis (Castor) Seed Oil, Sodium hydroxide, Sorbitan stearate.

Questions or Comments

1 866-516-5508 or Support@ProloGel.com

PRINCIPAL DISPLAY PANEL - 148 mL Bottle Carton

ProloGel®

URGENT CARE
FORMULA

For Rapid Relief
Deep Penetrating
Vanishing Odor

Topical Therapeutic Lotion

Net Wt. 5 oz / 148 mL